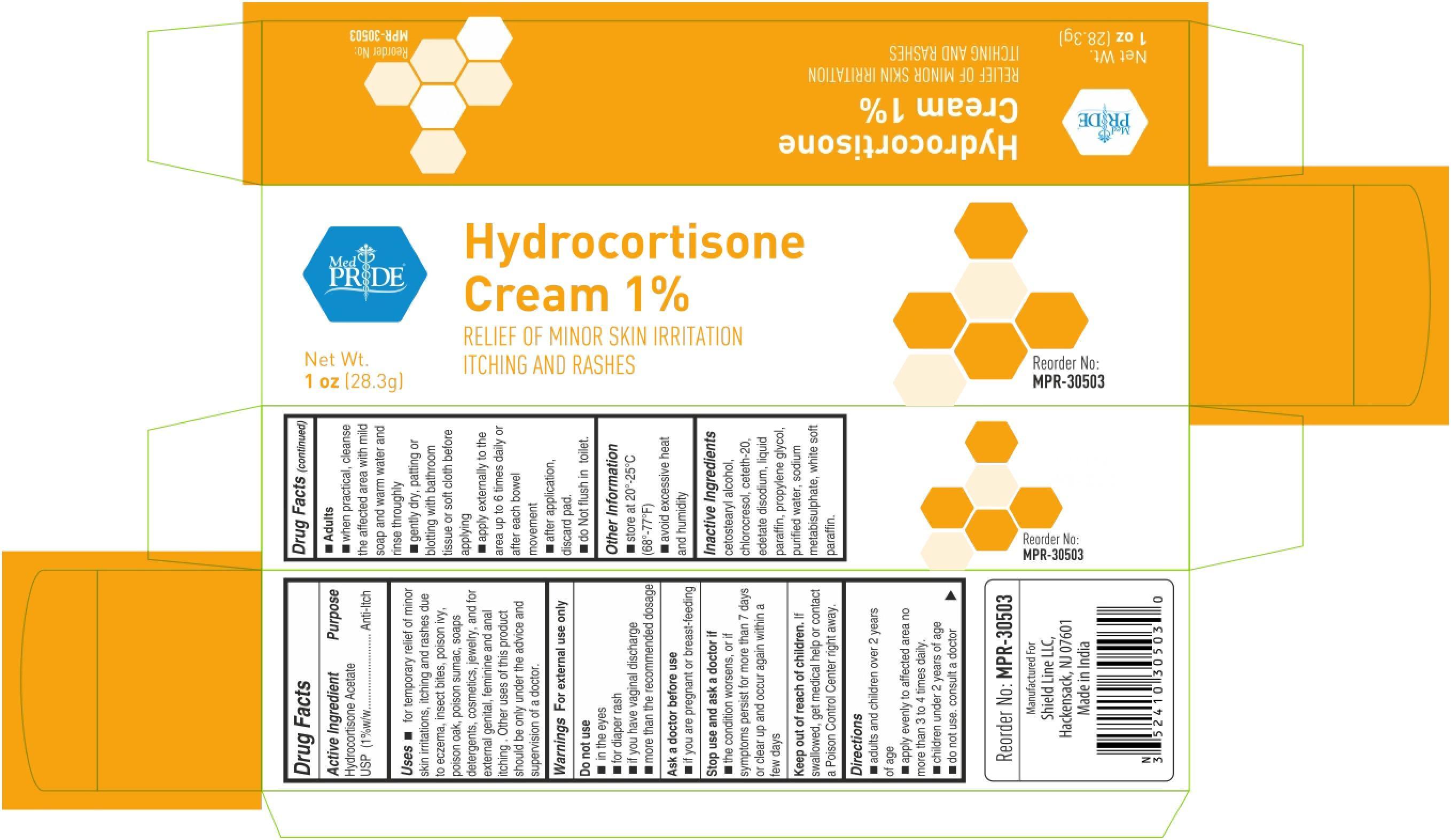 DRUG LABEL: MedPride
NDC: 52410-3050 | Form: CREAM
Manufacturer: Shield Line LLC
Category: otc | Type: HUMAN OTC DRUG LABEL
Date: 20250815

ACTIVE INGREDIENTS: HYDROCORTISONE ACETATE 10 mg/1 g
INACTIVE INGREDIENTS: CETOSTEARYL ALCOHOL; CHLOROCRESOL; CETETH-20; EDETATE DISODIUM; MINERAL OIL; PROPYLENE GLYCOL; WATER; SODIUM METABISULFITE; PETROLATUM

MedPride Hydrocortisone

Active Ingredient

Hydrocortisone Acetate USP (1% w/w)

Purpose

Anti-itch

Uses

■ for temporary relief of minor skin irritations, itching and rashes due to eczema, insect bites, poison ivy, poison oak, poison sumac, soaps, detergents, cosmetics, jewelry, and for external genital, feminine and anal itching. Other uses of this product should be only under the advice and supervision of a doctor

Warnings

For external use only

Do not use

■ in the eyes ■ for diaper rash ■ if you have vaginal discharge ■ more than the recommended dosage

Ask a doctor before use

■ if you are pregnant or breast feeding

Stop use and ask a doctor if

■ the condition worsens, or if symptoms persist for more than 7 days or clear up and occur again wihin a few days

Keep out of reach of children. If swallowed, get medical help or contact a Poison Control Center right away

Directions

■ adults and children over 2 years of age

■ apply evenly to affected area no more than 3 to 4 times daily

■ children under 2 years of age

■ do not use, consult a doctor

■ adults and children over 2 years of age

■ apply evenly to affected area no more than 3 to 4 times daily

■ children under 2 years of age

■ do not use, consult a doctor

■ Adults

■ when practical, cleanse the affected area with mild soap and warm water and rinse thoroughly

■ gently dry, patting or blotting with bathroom tissue or soft cloth before applying

■ apply externally to the area up to 6 times a daily or after a bowel movement

■ after application discard pad

■ do not flush in toilet

Other information

■ store at 20-25C (68-77F)

■ avoid excessive heat and humidity

Inactive Ingredients

cetostearyl alcohol, chlorocresol, ceteth-20, edetate disodium, liquid paraffin, propylene glycol, purified water, sodium metabisulphite, White white soft paraffin